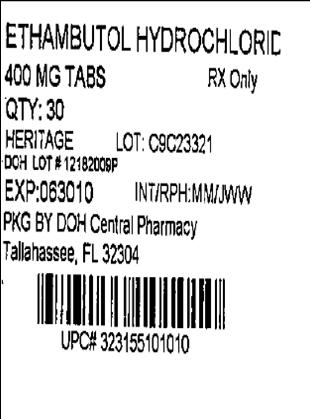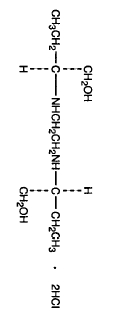 DRUG LABEL: Ethambutol Hydrochloride
NDC: 53808-0977 | Form: TABLET
Manufacturer: State of Florida DOH Central Pharmacy
Category: prescription | Type: HUMAN PRESCRIPTION DRUG LABEL
Date: 20100525

ACTIVE INGREDIENTS: ETHAMBUTOL HYDROCHLORIDE 400 mg/1 1
INACTIVE INGREDIENTS: SILICON DIOXIDE; SUCROSE; GELATIN; HYDROXYMETHYL CELLULOSE; MAGNESIUM STEARATE; POLYDEXTROSE; POLYETHYLENE GLYCOL; SODIUM LAURYL SULFATE; STEARIC ACID; TITANIUM DIOXIDE; TRIACETIN

ETHAMBUTOL HYDROCHLORIDE TABLETS, USP

Rx only

Description:

Ethambutol hydrochloride is an oral chemothera-peutic agent which is specifically effective against actively growing microorganisms of the genus Mycobacterium, including M. tuberculosis. It is a white, crystalline powder. Freely soluble in water; soluble in alcohol and in methanol; slightly soluble in ether and in chloroform. It has the chemical formula of: (+)-2,2’(Ethylenediimino)-di-1-butanol dihydrochloride. The structural formula is as follows:

C10H24N2O2·2HCl Molecular Weight: 277.23

Each tablet, for oral administration, contains 400 mg of ethambutol hydrochloride. In addition, each tablet contains the following inactive ingredients: colloidal silicon dioxide, compressible sugar, gelatin, hydroxypropyl methylcellulose, magnesium stearate, methylcellulose, polydextrose, polyethylene glycol, sodium lauryl sulfate, stearic acid, titanium dioxide, and triacetin.

Clinical Pharmacology:

Ethambutol hydrochloride following a single oral dose of 25 mg/kg of body weight, attains a peak of 2 to 5 micrograms/mL in serum 2 to 4 hours after administration. When the drug is administered daily for longer periods of time at this dose, serum levels are similar. The serum level of ethambutol hydrochloride falls to undetectable levels by 24 hours after the last dose except in some patients with abnormal renal function. The intracellular concentrations of erythrocytes reach peak values approximately twice those of plasma and maintain this ratio throughout the 24 hours.

During the 24-hour period following oral administration of ethambutol hydrochloride approximately 50 percent of the initial dose is excreted unchanged in the urine, while an additional 8 to 15 percent appears in the form of metabolites. The main path of metabolism appears to be an initial oxidation of the alcohol to an aldehydic intermediate, followed by conversion to a dicarboxylic acid. From 20 to 22 percent of the initial dose is excreted in the feces as unchanged drug. No drug accumulation has been observed with consecutive single daily doses of 25 mg/kg in patients with normal kidney function, although marked accumulation has been demonstrated in patients with renal insufficiency.

Ethambutol diffuses into actively growing mycobacterium cells such as tubercle bacilli. Ethambutol appears to inhibit the synthesis of one or more metabolites, thus causing impairment of cell metabolism, arrest of multiplication, and cell death. No cross resistance with other available antimycobacterial agents has been demonstrated.

Ethambutol has been shown to be effective against strains of Mycobacterium tuberculosis but does not seem to be active against fungi, viruses, or other bacteria. Mycobacterium tuberculosis strains previously unexposed to ethambutol have been uniformly sensitive to concentrations of 8 or less micrograms/mL, depending on the nature of the culture media. When ethambutol has been used alone for treatment of tuberculosis, tubercle bacilli from these patients have developed resistance to ethambutol hydrochloride by in vitro susceptibilty tests; the development of resistance has been unpredictable and appears to occur in a step-like manner. No cross resistance between ethambutol and other antituberculous drugs has been reported. Ethambutol has reduced the incidence of the emergence of mycobacterial resistance to isoniazid when both drugs have been used concurrently.

An agar diffusion microbiologic assay, based upon inhibition of Mycobacterium smegmatis (ATCC 607) may be used to determine concentrations of ethambutol in serum and urine.

ANIMAL PHARMACOLOGY:

Toxicological studies in dogs on high prolonged doses produced evidence of myocardial damage and failure, and depigmentation of the tapetum lucidum of the eyes, the significance of which is not known. Degenerative changes in the central nervous system, apparently not dose-related, have also been noted in dogs receiving ethambutol hydrochloride over a prolonged period.

In the rhesus monkey, neurological signs appeared after treatment with high doses given daily over a period of several months. These were correlated with specific serum levels of ethambutol hydrochloride and with definite neuroanatomical changes in the central nervous system. Focal interstitial carditis was also noted in monkeys which received ethambutol hydrochloride in high doses for a prolonged period.

When pregnant mice or rabbits were treated with high doses of ethambutol hydrochloride, fetal mortality was slightly but not significantly (P>0.05) increased. Female rats treated with ethambutol hydrochloride displayed slight but insignificant (P>0.05) decreases in fertility and litter size.

In fetuses born of mice treated with high doses of ethambutol hydrochloride during pregnancy, a low incidence of cleft palate, exencephaly and abnormality of the vertebral column were observed. Minor abnormalities of the cervical vertebra were seen in the newborn of rats treated with high doses of ethambutol hydrochloride during pregnancy. Rabbits receiving high doses of ethambutol hydrochloride during pregnancy gave birth to two fetuses with monophthalmia, one with a shortened right forearm accompanied by bilateral wrist-joint contracture and one with hare lip and cleft palate.

Indications and Usage:

Ethambutol Hydrochloride Tablets are indicated for the treatment of pulmonary tuberculosis. It should not be used as the sole antituberculous drug, but should be used in conjunction with at least one other antituberculous drug. Selection of the companion drug should be based on clinical experience, considerations of comparative safety and appropriate in vitro susceptibility studies.

In patients who have not received previous antituberculous therapy, i.e., initial treatment, the most frequently used regimens have been the following:

Ethambutol plus isoniazid

Ethambutol plus isoniazid plus streptomycin.

In patients who have received previous antituberculous therapy, mycobacterial resistance to other drugs used in initial therapy is frequent.

Consequently, in such retreatment patients, ethambutol should be combined with at least one of the second line drugs not previously administered to the patient and to which bacterial susceptibility has been indicated by appropriate in vitro studies. Antituberculous drugs used with ethambutol have included cycloserine, ethionamide, pyrazinamide, viomycin, and other drugs. Isoniazid, aminosalicylic acid, and streptomycin have also been used in multiple drug regimens. Alternating drug regimens have also been utilized.

Contraindications:

Ethambutol hydrochloride is contraindicated in patients who are known to be hypersensitive to this drug. It is also contraindicated in patients with known optic neuritis unless clinical judgment determines that it may be used.

Precautions:

The effects of combinations of ethambutol hydrochloride with other antituberculous drugs on the fetus is not known. While administration of this drug to pregnant human patients has produced no detectable effect upon the fetus, the possible teratogenic potential in women capable of bearing children should be weighed carefully against the benefits of therapy. There are published reports of five women who received the drug during pregnancy without apparent adverse effect upon the fetus.

Ethambutol is not recommended for use in pediatric patients under thirteen years of age since safe conditions for use have not been established.

Patients with decreased renal function need the dosage reduced as determined by serum levels of ethambutol, since the main path of excretion of this drug is by the kidneys.

Because this drug may have adverse effects on vision, physical examination should include ophthalmoscopy, finger perimetry and testing of color discrimination. In patients with visual defects such as cataracts, recurrent inflammatory conditions of the eye, optic neuritis, and diabetic retinopathy, the evaluation of changes in visual acuity is more difficult, and care should be taken to be sure the variations in vision are not due to the underlying disease conditions. In such patients, consideration should be given to relationship between benefits expected and possible visual deterioration since evaluation of visual changes is difficult. (For recommended procedures, see next paragraphs under ADVERSE REACTIONS.)

As with any potent drug, periodic assessment of organ system functions, including renal, hepatic, and hematopoietic, should be made during long-term therapy.

Adverse Reactions:

Ethambutol may produce decreases in visual acuity which appear to be due to optic neuritis. This effect may be related to dose and duration of treatment. This effect is generally reversible when administration of the drug is discontinued promptly. In rare cases recovery may be delayed for up to one year or more. Irreversible blindness has been reported.

Optic neuropathy including optic neuritis or retrobulbar neuritis occurring in association with ethambutol therapy may be characterized by one or more of the following events: decreased visual acuity, scotoma, color blindness, and/or visual defect. These events have also been reported in the absence of a diagnosis of optic or retrobulbar neuritis.

Patients should be advised to report promptly to their physician any change of visual acuity.

The change in visual acuity may be unilateral or bilateral and hence each eye must be tested separately and both eyes tested together. Testing of visual acuity should be performed before beginning ethambutol hydrochloride therapy and periodically during drug administration, except that it should be done monthly when a patient is on a dosage of more than 15 mg per kilogram per day. Snellen eye charts are recommended for testing of visual acuity. Studies have shown that there are definite fluctuations of one or two lines of the Snellen chart in the visual acuity of many tuberculous patients not receiving ethambutol.

The following table may be useful in interpreting possible changes in visual acuity attributable to ethambutol.

Initial; Snellen; Reading | Reading; Indicating; Significant Decrease | Significant; Number; of Lines | Decrease; Number; of Points
20/13 | 20/25 | 3 | 12
20/15 | 20/25 | 2 | 10
20/20 | 20/30 | 2 | 10
20/25 | 20/40 | 2 | 15
20/30 | 20/50 | 2 | 20
20/40 | 20/70 | 2 | 30
20/50 | 20/70 | 1 | 20

In general, changes in visual acuity less than those indicated under "Significant Number of Lines" and "Decrease-Number of Points," may be due to chance variation, limitations of the testing method or physiologic variability. Conversely, changes in visual acuity equaling or exceeding those under "Significant Number of Lines" and "Decrease-Number of Points" indicate need for retesting and careful evaluation of the patient's visual status. If careful evaluation confirms the magnitude of visual change and fails to reveal another cause, ethambutol should be discontinued and the patient reevaluated at frequent intervals. Progressive decreases in visual acuity during therapy must be considered to be due to ethambutol.

If corrective glasses are used prior to treatment, these must be worn during visual acuity testing. During 1 to 2 years of therapy, a refractive error may develop which must be corrected in order to obtain accurate test results. Testing the visual acuity through a pinhole eliminates refractive error. Patients developing visual abnormality during ethambutol treatment may show subjective visual symptoms before, or simultaneously with, the demonstration of decreases in visual acuity, and all patients receiving ethambutol should be questioned periodically about blurred vision and other subjective eye symptoms.

Recovery of visual acuity generally occurs over a period of weeks to months after the drug has been discontinued. Some patients have received ethambutol hydrochloride again after such recovery without recurrence of loss of visual acuity.

Other adverse reactions reported include: anaphylactoid reactions, dermatitis, pruritus and joint pain; anorexia, nausea, vomiting, gastrointestinal upset, abdominal pain; fever, malaise, headache, and dizziness; mental confusion, disorientation and possible hallucinations. Numbness and tingling of the extremities due to peripheral neuritis have been reported infrequently.

Elevated serum uric acid levels occur and precipitation of acute gout has been reported. Pulmonary infiltrates and eosinophilia also have been reported during ethambutol hydrochloride therapy. Transient impairment of liver function as indicated by abnormal liver function tests is not an unusual finding. Since ethambutol is recommended for therapy in conjunction with one or more other antituberculous drugs, these changes may be related to the concurrent therapy.

Dosage and Administration:

Ethambutol hydrochloride should not be used alone, in initial treatment or in retreatment. Ethambutol hydrochloride should be administered on a once every 24-hour basis only. Absorption is not significantly altered by administration with food. Therapy, in general, should be continued until bacteriological conversion has become permanent and maximal clinical improvement has occurred.

Ethambutol hydrochloride is not recommended for use in pediatric patients under thirteen years of age since safe conditions for use have not been established.

Initial Treatment:

In patients who have not received previous antituberculous therapy, administer ethambutol hydrochloride 15 mg per kilogram (7 mg per pound) of body weight, as a single oral dose once every 24 hours. In the more recent studies, isoniazid has been administered concurrently in a single, daily, oral dose.

Retreatment:

In patients who have received previous antituberculous therapy, administer ethambutol hydrochloride 25 mg per kilogram (11 mg per pound) of body weight, as a single oral dose once every 24 hours. Concurrently administer at least one other antituberculous drug to which the organisms have been demonstrated to be susceptible by appropriate in vitro tests. Suitable drugs usually consist of those not previously used in the treatment of the patient. After 60 days of ethambutol hydrochloride administration, decrease the dose to 15 mg per kilogram (7 mg per pound) of body weight, and administer as a single oral dose once every 24 hours.

During the period when a patient is on a daily dose of 25 mg/kg, monthly eye examinations are advised.

See Table for easy selection of proper weight-dose tablet(s).

Weight-Dose Table
15 mg/kg (7 mg/lb) Schedule
Weight Range |  | Daily Dose
Pounds | Kilograms | In mg
Under 85 lbs | Under 37 kg | 500
85-94.5 | 37-43 | 600
95-109.5 | 43-50 | 700
110-124.5 | 50-57 | 800
125-139.5 | 57-64 | 900
140-154.5 | 64-71 | 1000
155-169.5 | 71-79 | 1100
170-184.5 | 79-84 | 1200
185-199.5 | 84-90 | 1300
200-214.5 | 90-97 | 1400
215 and Over | Over 97 | 1500
25 mg/kg (11 mg/lb) Schedule
Under 85 lbs | Under 38 kg | 900
85-92.5 | 38-42 | 1000
93-101.5 | 42-45.5 | 1100
102-109.5 | 45.5-50 | 1200
110-118.5 | 50-54 | 1300
119-128.5 | 54-58 | 1400
129-136.5 | 58-62 | 1500
137-146.5 | 62-67 | 1600
147-155.5 | 67-71 | 1700
156-164.5 | 71-75 | 1800
165-173.5 | 75-79 | 1900
174-182.5 | 79-83 | 2000
183-191.5 | 83-87 | 2100
192-199.5 | 87-91 | 2200
200-209.5 | 91-95 | 2300
210-218.5 | 95-99 | 2400
219 and Over | Over 99 | 2500

How Supplied:

Ethambutol Hydrochloride Tablets, USP are supplied by State of Florida DOH Central Pharmacy as follows:

NDC | Strength | Quantity/Form | Color | Source Prod. Code
53808-0977-1 | 400 mg | 30 Tablets in a Blister Pack | WHITE | 23155-0101

Store at controlled room temperature 15°-30°C (59°-86°F) [see USP].

MANUFACTURED BY

Heritage

COLUMBIA, MD

This Product was Repackaged By:

State of Florida DOH Central Pharmacy
104-2 Hamilton Park Drive
Tallahassee, FL 32304
United States